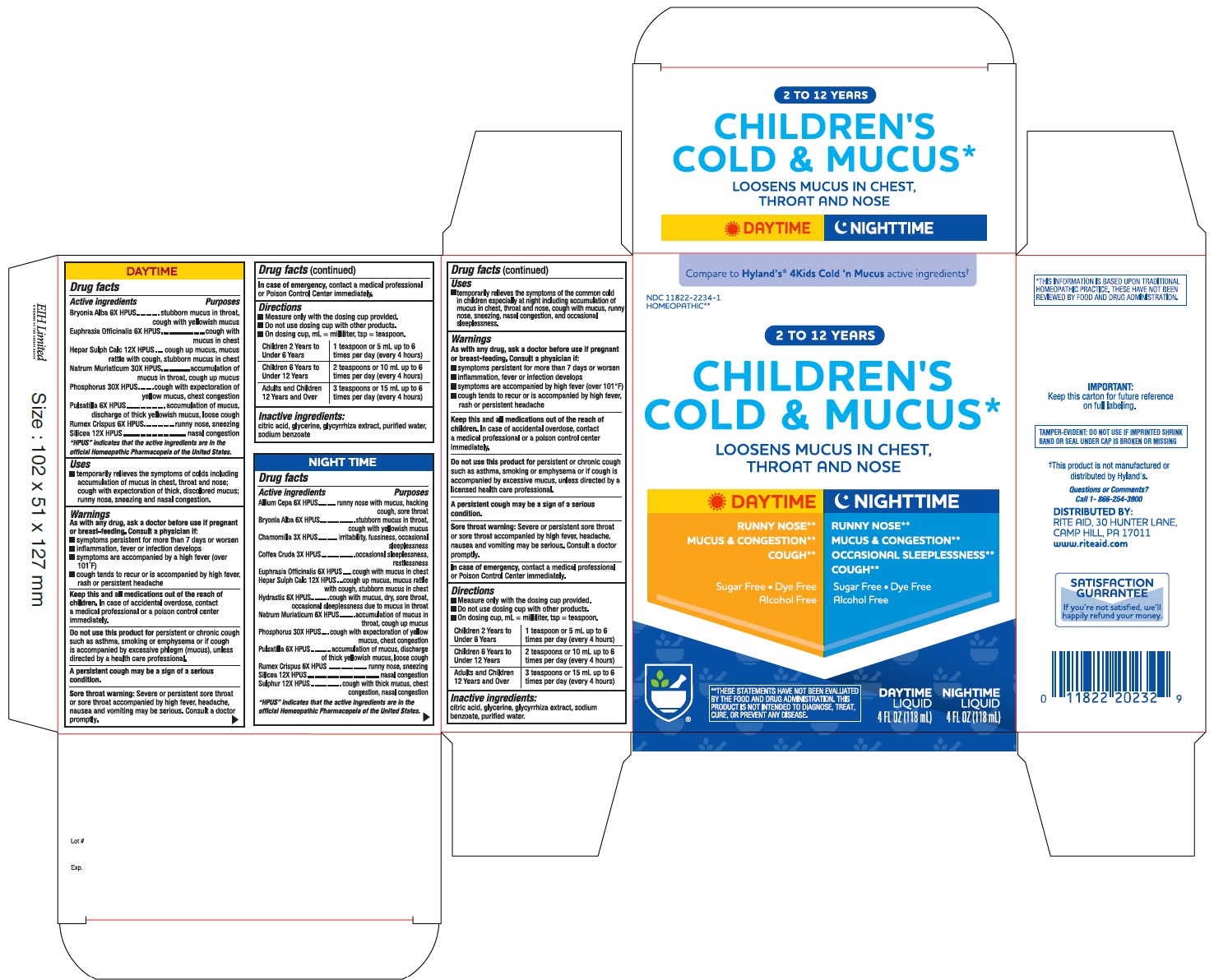 DRUG LABEL: 2 to 12 YEARS CHILDRENS COLD and MUCUS
NDC: 11822-2234 | Form: KIT | Route: ORAL
Manufacturer: Rite Aid Hdgrts Corp
Category: homeopathic | Type: HUMAN OTC DRUG LABEL
Date: 20241227

ACTIVE INGREDIENTS: MATRICARIA CHAMOMILLA 3 [hp_X]/1 mL; SODIUM CHLORIDE 6 [hp_X]/1 mL; SULFUR 12 [hp_X]/1 mL; RUMEX CRISPUS ROOT 6 [hp_X]/1 mL; ONION 6 [hp_X]/1 mL; BRYONIA ALBA ROOT 6 [hp_X]/1 mL; EUPHRASIA STRICTA 6 [hp_X]/1 mL; GOLDENSEAL 6 [hp_X]/1 mL; PHOSPHORUS 30 [hp_X]/1 mL; ARABICA COFFEE BEAN 3 [hp_X]/1 mL; CALCIUM SULFIDE 12 [hp_X]/1 mL; SILICON DIOXIDE 12 [hp_X]/1 mL; ANEMONE PULSATILLA 6 [hp_X]/1 mL; EUPHRASIA STRICTA 6 [hp_X]/1 mL; BRYONIA ALBA ROOT 6 [hp_X]/1 mL; ANEMONE PULSATILLA 6 [hp_X]/1 mL; SODIUM CHLORIDE 30 [hp_X]/1 mL; PHOSPHORUS 30 [hp_X]/1 mL; SILICON DIOXIDE 12 [hp_X]/1 mL; RUMEX CRISPUS ROOT 6 [hp_X]/1 mL; CALCIUM SULFIDE 12 [hp_X]/1 mL
INACTIVE INGREDIENTS: GLYCYRRHIZA GLABRA; SODIUM BENZOATE; WATER; CITRIC ACID MONOHYDRATE; GLYCERIN; SODIUM BENZOATE; GLYCERIN; WATER; CITRIC ACID MONOHYDRATE; GLYCYRRHIZA GLABRA

2 to 12 YEARS
CHILDREN'S COLD & MUCUS DAY & NIGHT TIME
LOOSENS MUCUS IN CHEST, THROAT AND NOSE

DAYTIME

Drug Facts

Active ingredients Purposes

Bryonia Alba 6X HPUS ................................. stubborn mucus in throat, cough with yellowish mucus
Euphrasia Officinalis 6X HPUS ..................... cough with mucus in chest
Hepar Sulph Calc 12X HPUS ......................... cough up mucus, mucus rattle with cough, stubborn mucus in chest
Natrum Muriaticum 30X HPUS .................... .accumulation of mucus in throat, cough up mucus
Phosphorus 30X HPUS .................................. cough with expectoration of yellow mucus, chest congestion
Pulsatilla 6X HPUS ........................................ accumulation of mucus, discharge of thick yellowish mucus, loose cough
Rumex Crispus 6X HPUS .............................. runny nose, sneezing
Silicea 12X HPUS ......................................... nasal congestion

“HPUS” indicates that the active ingredients are in the official Homeopathic Pharmacopoeia of the United States.

PURPOSE

LOOSENS MUCUS IN CHEST, THROAT AND NOSE

Uses

- Temporarily relieves the symptoms of colds including accumulation of mucus in chest, throat and nose; cough with expectoration of thick, discolored mucus; runny nose, sneezing and nasal congestion.

Warnings

PREGNANCY OR BREAST FEEDING

As with any drug, ask a doctor before use if pregnant or breast-feeding.

ASK DOCTOR

Consult a physician if:

- symptoms persist for more than 7 days or worsen.
- inflammation, fever or infection develops.
- symptoms are accompanied by a high fever (over 101°F).
- cough tends to recur or is accompanied by a high fever,rash or persistent headache.

KEEP OUT OF REACH OF CHILDREN

Keep this and all medications out of the reach of children. In case of accidental overdose, contact a medical professional or Poison Control Center immediately.

Do not use this product for persistent or chronic cough such as asthma, smoking or emphysema or if cough is accompanied by excessive phlegm (mucus), unless directed by a licensed health care professional.

A persistent cough may be a sign of a serious condition.

Sore throat warning

Severe or persistent sore throat or sore throat accompanied by high fever, headache, nausea, and vomiting may be serious. Consult a doctor promptly.

In case of emergency, contact a medical professional or Poison Control Center immediately.

Drug Facts (continued)

Directions

- Measure only with the dosing cup provided
- Do not use dosing cup with other products
- On dosing cup, mL = milliliter, tsp = teaspoon

Children 2 years; to under 6 years | 1 teaspoon or 5 mL up to; 6 times per day (every 4 hours)
Children 6 years; to under 12 years | 2 teaspoons or 10 mL up to; 6 times per day (every 4 hours)
Adults and children; 12 years and over | 3 teaspoons or 15 mL up to; 6 times per day (every 4 hours)

Inactive ingredients

Citric Acid, Glycerin, Glycyrrhiza Extract, Purified Water, Sodium Benzoate.

NIGHTTIME

Active ingredients Purposes

Allium Cepa 6X HPUS ..................... runny nose with mucus, hacking cough, sore throat
Bryonia Alba 6X HPUS .................... stubborn mucus in throat, cough wilh yellowish mucus
Chamomilla 3X HPUS ..................... irritabilily, fussiness, occasional sleeplessness
Collea Cruda 3X HPUS .................... occasional sleeplessness, restlessness
Euphrasia Officinalis 6X HPUS .......... cough with mucus in chest
Hepar Sulph Calc 12X HPUS .............. cough up mucus, mucus rattle with cough, stubborn mucus in chest
Hydrastis 6X HPUS ........................... cough with mucus, dry, sore throat, occasional sleeplessness due to mucus in throat
Natrum Muriaticum 6X HPUS ............ accumulation of mucus in throat, cough up mucus
Phosphorus 30X HPUS ...................... cough with expectoration of yellow mucus, chest congestion
Pulsatilla 6X HPUS ........................... accumulation of mucus, discharge of thick yellowish mucus, loose cough
Rumex Crispus 6X HPUS ................... runny nose, sneezing
Silicea 12X HPUS ............................... nasal congestion
Sulphur 12X HPUS ............................ cough with thick mucus, chest congestion, nasal congestion

“HPUS” indicates that the active ingredients are in the official Homeopathic Pharmacopœia of the United States.

PURPOSE

LOOSENS MUCUS IN CHEST, THROAT AND NOSE

Uses

- Temporarily relieves the symptoms of the common cold in children especially at mght including accumulation of mucus in chest, throat and nose, cough with mucus, runny nose, sneezing, nasal congestion, and occasional sleeplessness.

Drug Facts (continued)

Warnings

PREGNANCY OR BREAST FEEDING

As with any drug, ask a doctor before use if pregnant or breast-feeding.

ASK DOCTOR

Consult a physician if:

- symptoms persist for more than 7 days or worsen.
- inflammation, fever or infection develops.
- symptoms are accompanied by a high fever (over 101°F).
- cough tends to recur or is accompanied by a high fever,rash or persistent headache.

KEEP OUT OF REACH OF CHILDREN

Keep this and all medications out of the reach of children. In case of accidental overdose, contact a medical professional or Poison Control Center immediately.

Do not use this product for persistent or chronic cough such as asthma, smoking or emphysema or if cough is accompanied by excessive mucus, unless directed by a licensed health care professional.

A persistent cough may be a sign of a serious condition.

Sore throat warning

Severe or persistent sore throat or sore throat accompanied by high fever, headache, nausea, and vomiting may be serious. Consult a doctor promptly.

In case of emergency, contact a medical professional or Poison Control Center immediately.

Directions

- Measure only with the dosing cup provided
- Do not use dosing cup with other products
- On dosing cup, mL = milliliter, tsp = teaspoon

Children 2 years; to under 6 years | 1 teaspoon or 5 mL up to; 6 times per day (every 4 hours)
Children 6 years; to under 12 years | 2 teaspoon or 10 mL up to; 6 times per day (every 4 hours)
Adults and children; 12 years and over | 3 teaspoon or 15 mL up to; 6 times per day (every 4 hours)

Inactive ingredients

Citric Acid, Glycerin, Glycyrrhiza Extract, Purified Water, Sodium Benzoate.

Questions or comments?
Call 1-866-254-3900.

- THIS INFORMATION IS BASED UPON TRADITIONAL HOMEOPATHIC PRACTICE. THESE HAVE NOT BEEN REVIEWED BY FOOD AND DRUG ADMINISTRATION
- TAMPER-EVIDENT: DO NOT USE IF IMPRINTED SHRINK BAND OR SEAL UNDER CAP IS BROKEN OR MISSING
- This product is not manufactured or distributed by Hyland's

Distributed by:

RITE AID, 30 HUNTER LANE,
CAMP HILL, PA 17011
www.riteaid.com

Principal Display Panel

CHILDREN'S COLD & MUCUS

Sugar Free, Dye Free

Alcohol free

DAYTIME

Runny Nose
Mucus & Congestion
Cough

NIGHTTIME

Runny Nose
Mucus & Congestion
Occasional Sleeplessness
Cough

2-12 YEARS

TWO - 4 FL. OZ. (118 mL) Bottles (1 Day, 1 Night)

HOMEOPATHIC